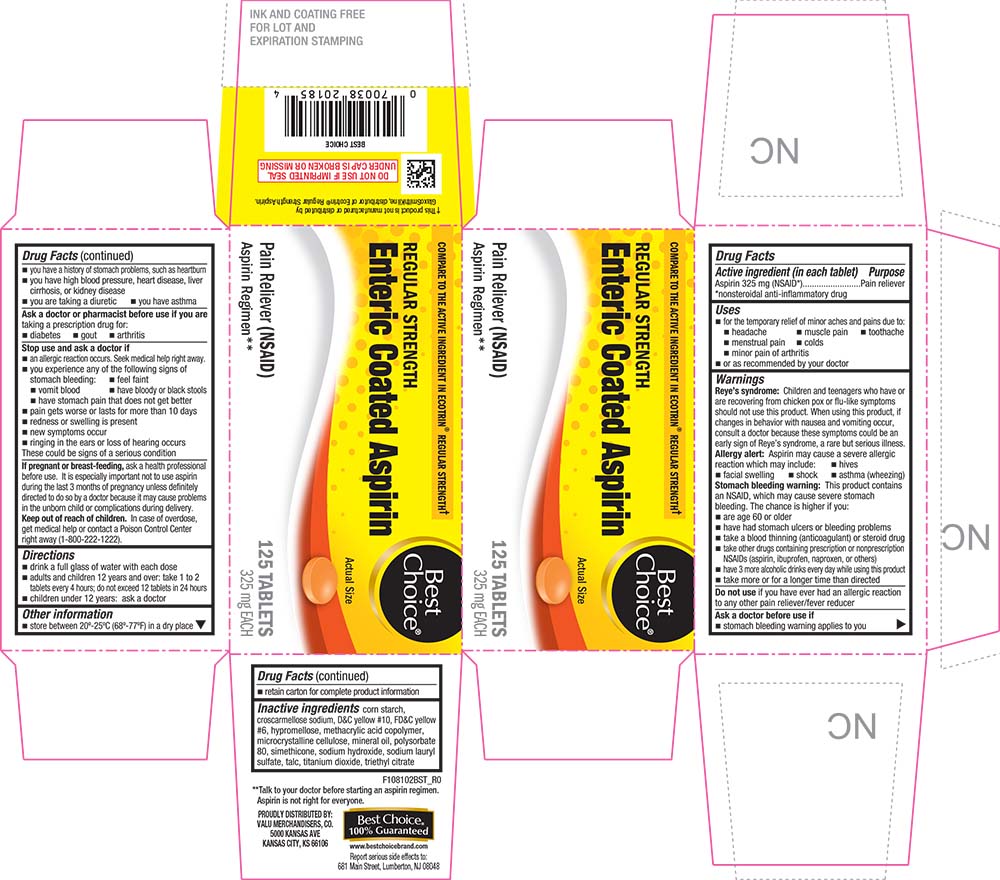 DRUG LABEL: Enteric Coated Aspirin
NDC: 63941-181 | Form: TABLET, DELAYED RELEASE
Manufacturer: VALU MERCHANDISERS COMPANY
Category: otc | Type: HUMAN OTC DRUG LABEL
Date: 20251211

ACTIVE INGREDIENTS: ASPIRIN 325 mg/1 1
INACTIVE INGREDIENTS: STARCH, CORN; CROSCARMELLOSE SODIUM; D&C YELLOW NO. 10; FD&C YELLOW NO. 6; HYPROMELLOSES; METHACRYLIC ACID - METHYL METHACRYLATE COPOLYMER (1:1); CELLULOSE, MICROCRYSTALLINE; MINERAL OIL; POLYSORBATE 80; DIMETHICONE; SODIUM HYDROXIDE; SODIUM LAURYL SULFATE; TALC; TITANIUM DIOXIDE; TRIETHYL CITRATE

1081-BST-2021-1116

Drug Facts

Active ingredient (in each tablet)

Aspirin 325 mg (NSAID [nonsteroidal anti-inflammatory drug])

Purpose

Pain reliever

Uses

- for the temporary relief of minor aches and pains due to:
  - headache
  - muscle pain
  - toothache
  - menstrual pain
  - colds
  - minor pain of arthritis
- or as recommended by your doctor

Warnings

Reye's syndrome

Children and teenagers who have or are recovering from chicken pox or flu-like symptoms should not use this product. When using this product, if changes in behavior with nausea and vomiting occur, consult a doctor because these symptoms could be an early sign of Reye's syndrome, a rare but serious illness.

Allergy alert

Aspirin may cause a severe allergic reaction which may include:

- hives
- facial swelling
- shock
- asthma (wheezing)

Stomach bleeding warning

This product contains an NSAID, which may cause severe stomach bleeding. The chance is higher if you:

- are age 60 or older
- have had stomach ulcers or bleeding problems
- take a blood thinning (anticoagulant) or steroid drug
- take other drugs containing prescription or nonprescription NSAIDs (aspirin, ibuprofen, naproxen, or others)
- have 3 more alcoholic drinks every day while using this product
- take more or for a longer time than directed

Do not use if you have ever had an allergic reaction to any other pain reliever/fever reducer

Ask a doctor before use if

- stomach bleeding warning applies to you
- you have a history of stomach problems, such as heartburn
- you have high blood pressure, heart disease, liver cirrhosis, or kidney disease
- you are taking a diuretic
- you have asthma

Ask a doctor or pharmacist before use if you are taking a prescription drug for:

- diabetes
- gout
- arthritis

Stop use and ask a doctor if

- an allergic reaction occurs. Seek medical help right away.
- you experience any of the following signs of stomach bleeding:
  - feel faint
  - vomit blood
  - have bloody or black stools
  - have stomach pain that does not get better
- pain gets worse or lasts for more than 10 days
- redness or swelling is present
- new symptoms occur
- ringing in the ears or loss of hearing occurs

These could be signs of a serious condition

PREGNANCY OR BREAST FEEDING

If pregnant or breast-feeding, ask a health professional before use. It is especially important not to use aspirin during the last 3 months of pregnancy unless definitely directed to do so by a doctor because it may cause problems in the unborn child or complications during delivery.

Keep out of reach of children. In case of overdose, get medical help or contact a Poison Control Center right away (1-800-222-1222).

Directions

- drink a full glass of water with each dose
- adults and children 12 years and over: take 1 to 2 tablets every 4 hours; do not exceed 12 tablets in 24 hours
- children under 12 years: ask a doctor

Other information

- store between 20°-25°C (68°-77°F) in a dry place
- retain carton for complete product information

Inactive ingredients

corn starch, croscarmellose sodium, D&C yellow #10, FD&C yellow #6, hypromellose, methacrylic acid copolymer, microcrystalline cellulose, mineral oil, polysorbate 80, simethicone, sodium hydroxide, sodium lauryl sulfate, talc, titanium dioxide, triethyl citrate

PRINCIPAL DISPLAY PANEL

COMPARE TO THE ACTIVE INGREDIENT IN ECOTRIN® REGULAR STRENGTH†

Best Choice®

REGULAR STRENGTH

Enteric Coated Aspirin

Actual Size

Pain Reliever (NSAID)

Aspirin Regimen**

125 TABLETS

325 mg EACH